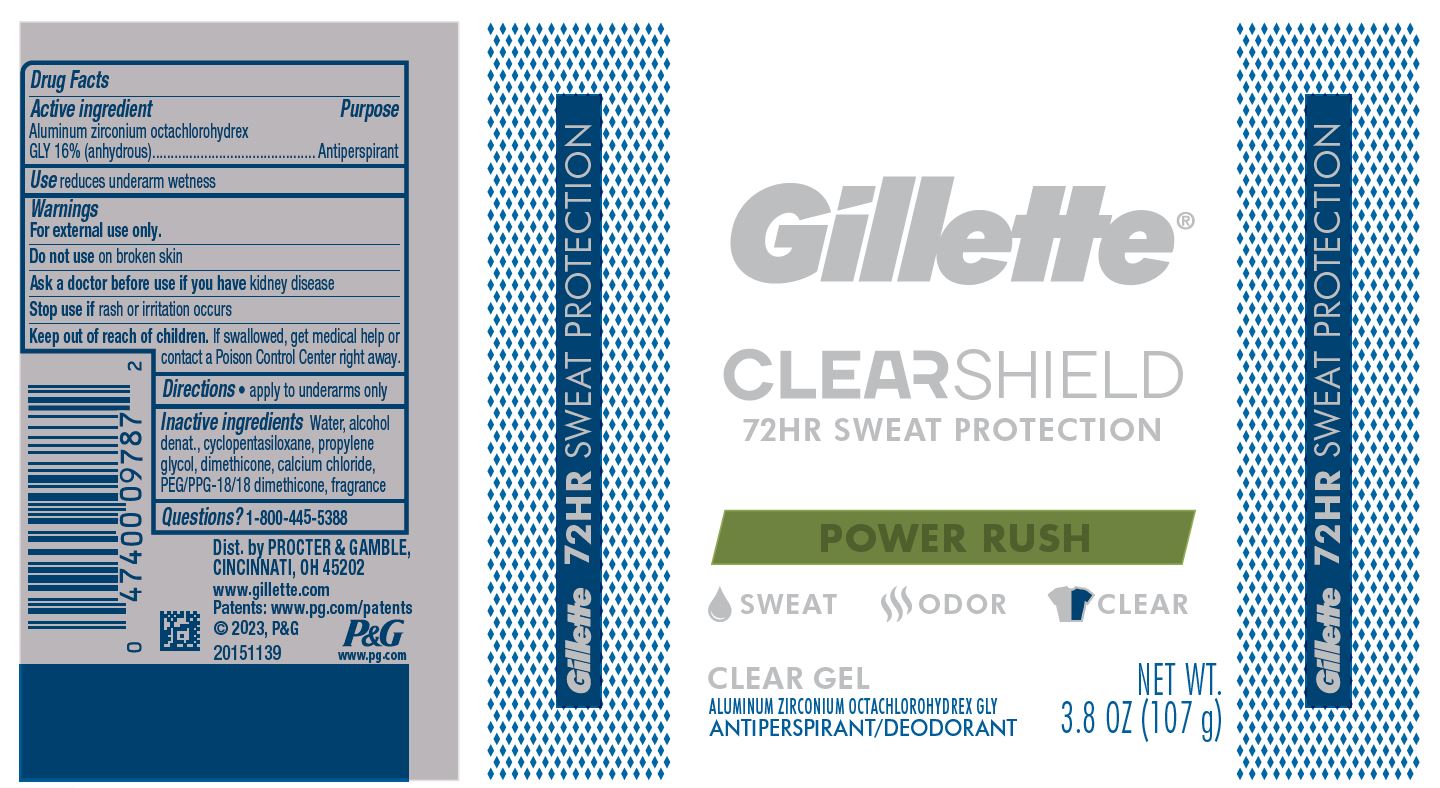 DRUG LABEL: Gillette ClearShield Power Rush Clear
NDC: 84126-016 | Form: GEL
Manufacturer: The Procter & Gamble Manufacturing Company
Category: otc | Type: HUMAN OTC DRUG LABEL
Date: 20260225

ACTIVE INGREDIENTS: ALUMINUM ZIRCONIUM OCTACHLOROHYDREX GLY 16 g/100 g
INACTIVE INGREDIENTS: ALCOHOL; WATER; CYCLOMETHICONE 5; PROPYLENE GLYCOL; DIMETHICONE; CALCIUM CHLORIDE; PEG/PPG-18/18 DIMETHICONE

Gillette® ClearShield Power Rush Clear Gel (lower strength)

Drug Facts

Active ingredient

Aluminum zirconium octachlorohydrex Gly 16% (anhydrous)

Purpose

Antiperspirant

Use

reduces underarm wetness

Warnings

For external use only.

Do not use on broken skin

Ask a doctor before use if you have kidney disease

Stop use if rash or irritation occurs

Keep out of reach of children. If swallowed, get medical help or contact a Poison Control Center right away.

Directions

- apply to underarms only

Inactive ingredients

water, alcohol denat., cyclopentasiloxane, propylene glycol, dimethicone, calcium chloride, PEG/PPG-18/18 dimethicone, fragrance

Questions?

1-800-445-5388

Dist. by PROCTER & GAMBLE,
CINCINNATI, OH 45202.

PACKAGE LABEL

Gillette ®
CLEARSHIELD

72HR SWEAT PROTECTION

POWER RUSH

CLEAR GEL

ALUMINUM ZIRCONIUM OCTACHLOROHYDREX GLY

ANTIPERSPIRANT/DEODORANT

NET WT. 3.8 OZ (107 g)